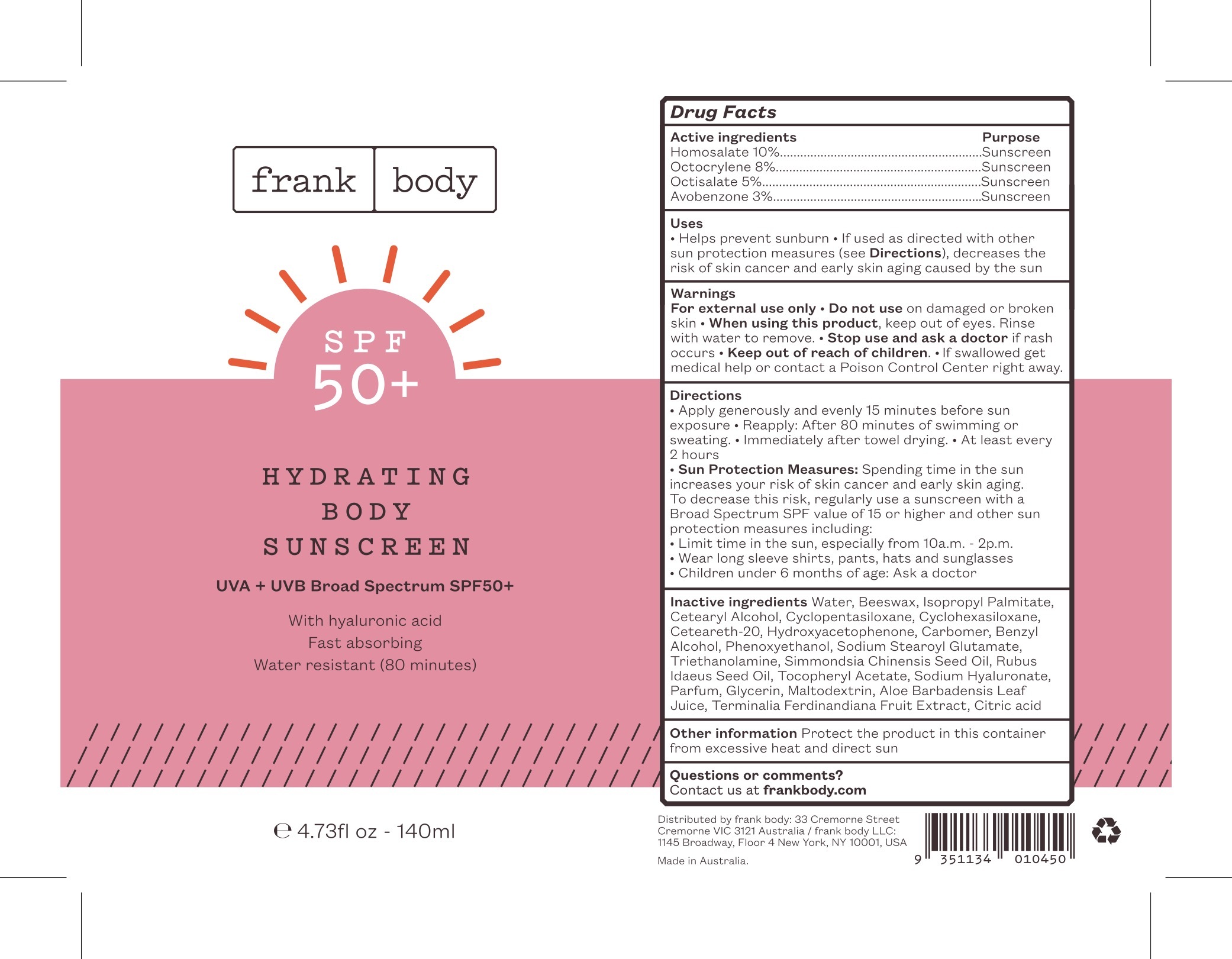 DRUG LABEL: Hydrating Body Sunscreen UVA and UVB Broad Spectrum SPF50
NDC: 70157-009 | Form: CREAM
Manufacturer: Baxter Laboratories Pty. Ltd.
Category: otc | Type: HUMAN OTC DRUG LABEL
Date: 20241018

ACTIVE INGREDIENTS: HOMOSALATE 10 g/100 mL; OCTOCRYLENE 8 g/100 mL; AVOBENZONE 3 g/100 mL; OCTISALATE 5 g/100 mL
INACTIVE INGREDIENTS: CYCLOMETHICONE 6; HYALURONATE SODIUM; MALTODEXTRIN; KAKADU PLUM; CITRIC ACID MONOHYDRATE; CARBOMER HOMOPOLYMER, UNSPECIFIED TYPE; HYDROXYACETOPHENONE; WATER; ISOPROPYL PALMITATE; BENZYL ALCOHOL; TROLAMINE; POLYOXYL 20 CETOSTEARYL ETHER; YELLOW WAX; CETOSTEARYL ALCOHOL; CYCLOMETHICONE 5; PHENOXYETHANOL; SODIUM STEAROYL GLUTAMATE; JOJOBA OIL; RASPBERRY SEED OIL; ALOE VERA LEAF; .ALPHA.-TOCOPHEROL ACETATE; GLYCERIN

Hydrating Body Sunscreen UVA and UVB Broad Spectrum SPF50

Active ingredients Purpose

Homosalate 10% .............Sunscreen

Octocrylene 8% ...............Sunscreen

Octisalate 5% ..................Sunscreen

Avobenzone 3% ..............Sunscreen

Uses

- Helps prevent sunburn
- If used as directed with other sun protection measures (see DIrections), decreases the risk of skin cancer and early skin aging caused by the sun

Keep our of reach of children.

Stop use and ask a doctor if rash occurs

Warnings

- For external use only
- Do not use on damaged or broken skin
- When using this product, keep out of eyes. RInse with water to remove.
- If swallowed get medical help or contact a Poison Control Center right away.

Directions

- Apply generously and evenly 15 minutes before sun exposure
- Reapply: After 80 minutes of swimming or sweating
- Immediately after towel drying
- At least every 2 hours
- Sun Protection Measures: Spending time in the sun increases your risk of skin cancer and early skin aging. To decrease this risk, regularly use a sunscreen with a Broad Spectrum SPF value of 15 or higher and other sun protection measures including:
- Limit time in the sun, especially from 10a.m.-2p.m.
- wear long sleeve shirts, pants, hats and sunglasses
- Children under 6 months of age: Ask a doctor

Inactive ingredients

Water, Beeswax, Isopropryl Palmitate, Cetearyl Alcohol, Cyclopentasiloxane, Cyclohexasiloxane, Ceteareth-20, Hydroxyacetophenone, Carbomer, Benzyl Alcohol, Phenoxyethanol, Sodium Stearoyl Glutamate, Triethanolamine, Simmondsia Chinensis Seed Oil, Rubus Idaeus Seed Oil, Tocopheryl Acetate, Sodium Hyaluronate, Parfum, Glycerin, Maltodextrin, Aloe Barbadensis Leaf Juice, Terminalia Ferdinandiana Fruit Extract, Citric Acid

OTHER SAFETY INFORMATION

Other informaiton Protect the product in this container from excessive heat and direct sun

Questions or comments?
Contact us at frankbody.com

PACKAGE LABEL

frank body

SPF 50+

Hydrating Body Sunscreen

UVA + UVB Broad Spectrum SPF50+

With hyaluronic acid

Fast absorbing

Water resistant (80 minutes)

4.73fl oz - 140ml